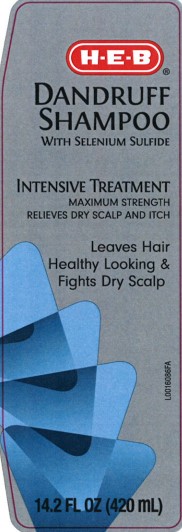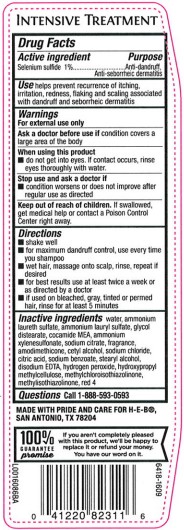 DRUG LABEL: Dandruff
NDC: 37808-816 | Form: SHAMPOO
Manufacturer: H E B
Category: otc | Type: HUMAN OTC DRUG LABEL
Date: 20260224

ACTIVE INGREDIENTS: SELENIUM SULFIDE 10 mg/1 mL
INACTIVE INGREDIENTS: WATER; AMMONIUM LAURETH-3 SULFATE; AMMONIUM LAURYL SULFATE; GLYCOL DISTEARATE; COCO MONOETHANOLAMIDE; AMMONIUM XYLENESULFONATE; SODIUM CITRATE; AMODIMETHICONE (800 CST); CETYL ALCOHOL; SODIUM CHLORIDE; CITRIC ACID MONOHYDRATE; SODIUM BENZOATE; STEARYL ALCOHOL; EDETATE DISODIUM; HYDROGEN PEROXIDE; HYPROMELLOSES; METHYLCHLOROISOTHIAZOLINONE; METHYLISOTHIAZOLINONE; FD&C RED NO. 4

HEB 816.000/816AC-AD
Advanced Solution Dandruff Shampoo

Claim

INTENSIVE TREATMENT

Active ingredient

Selenium sulfide 1%

Purpose

Anti-dandruff, Anti-seborrheic dermatitis

Use

helps prevent recurrence of itching, irritation, redness, flaking and scaling associated with dandruff and seborrheic dermatitis

Warnings

For external use only

Ask a doctor before use if

condition covers a large area of the body

When using this product

- do not get into eyes. If contact occurs, rinse eyes thoroughly with water.

Stop use and ask a doctor if

- condition worsens or does not improve after regular use as directed

Keep out of reach of children.

If swallowed, get medical help or contact a Poison Control Center right away.

Directions

- shake well
- for maximum dandruff control, use every time you shampoo
- wet hair, massage onto scalp, rinse, repeat if desired
- for best results use at least twice a week or as directed by a doctor
- if used on bleached, gray, tinted or permed hair, rinse for at least 5 minutes

Inactive ingredients

water, ammonium laureth sulfate, ammonium lauryl sulfate, glycol distearate, cocamide MEA, ammonium xylenesulfonate, sodium citrate, fragrance, amodimethicone, cetyl alcohol, sodium chloride, citric acid, sodium benzoate, stearyl alcohol, disodium EDTA, hydrogen peroxide, hydroxypropyl methylcellulose, methylchlorisothiazolinone, methylisothiazolinone, red 4

Questions

1-888-593-0593

ADVERSE REACTION

MADE WITH PRIDE AND CARE FOR H-E-B®, SAN ANTONIO, TX 78204

100% GUARANTEE promise - If you aren't completely pleased with this product, we'll be happy to replace it or refund your money.

You have our word on it.

principal display panel

H-E-B®

DANDRUFF SHAMPOO

With Selenium Sulfide

INTENSIVE TREATMENT

MAXIMUM STRENGTH

RELIEVES DRY SCALP AND ITCH

Leaves Hair Healthy Looking & Fights Dry Scalp

14.2 FL OZ (420 mL)